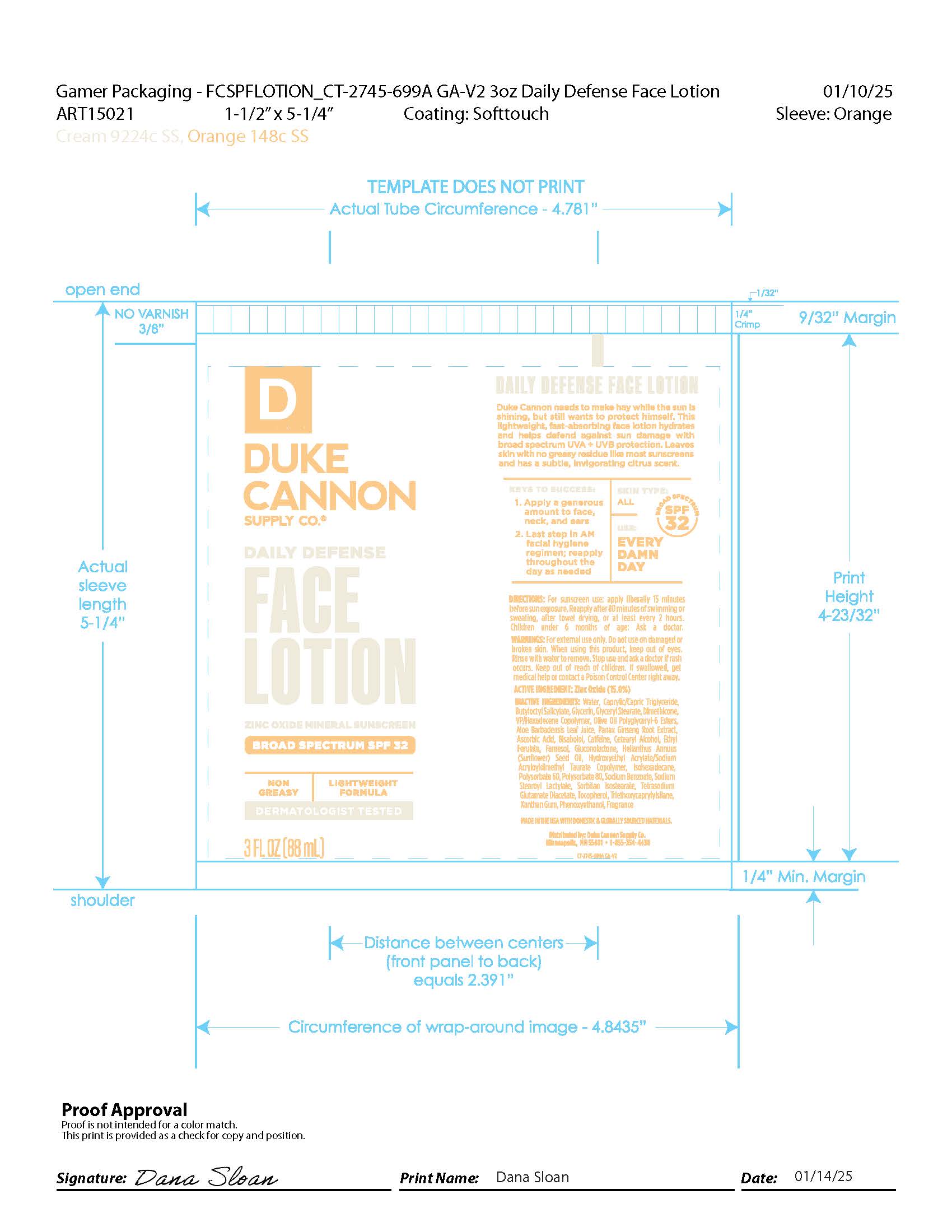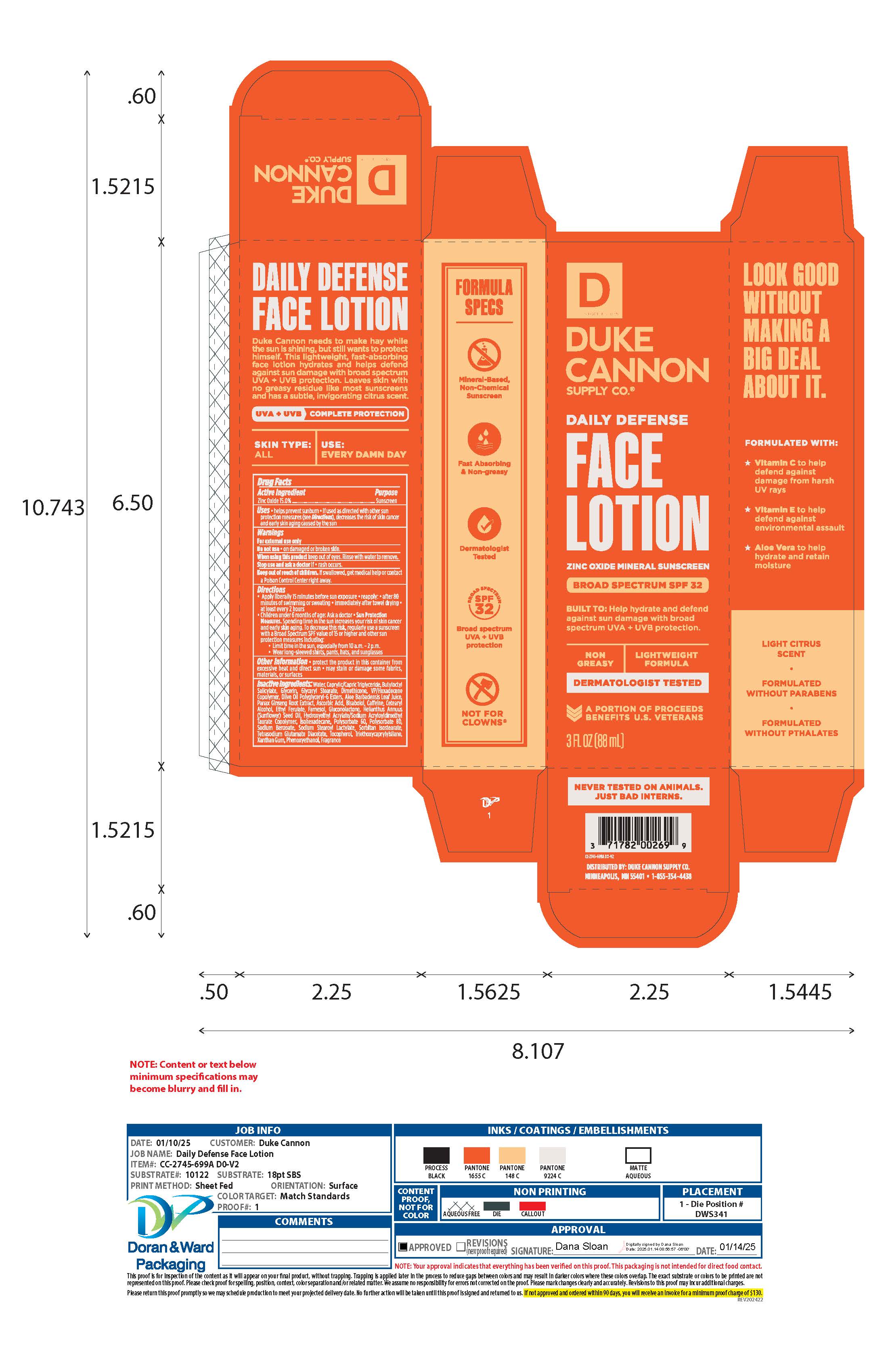 DRUG LABEL: Duke Cannon Supply Co. Daily Defense Face Mineral Sunscreen Broad Spectrum SPF 32
NDC: 71782-201 | Form: LOTION
Manufacturer: DUKE CANNON SUPPLY CO.
Category: otc | Type: HUMAN OTC DRUG LABEL
Date: 20251119

ACTIVE INGREDIENTS: ZINC OXIDE 150 mg/1 mL
INACTIVE INGREDIENTS: TETRASODIUM GLUTAMATE DIACETATE; SODIUM BENZOATE; GLYCERIN; PEG-20 SORBITAN ISOSTEARATE; CETOSTEARYL ALCOHOL; .ALPHA.-TOCOPHEROL, DL-; ASIAN GINSENG; ALOE VERA LEAF; BUTYLOCTYL SALICYLATE; CAFFEINE; ASCORBIC ACID; CAPRYLIC/CAPRIC ACID; WATER; POLYSORBATE 60; POLYSORBATE 80; BISABOLOL OXIDE A; ISOHEXADECANE; GLUCONOLACTONE; VINYLPYRROLIDONE/HEXADECENE COPOLYMER; SUNFLOWER OIL; XANTHAN GUM; ETHYL FERULATE; HYDROXYETHYL ACRYLATE/SODIUM ACRYLOYLDIMETHYL TAURATE COPOLYMER (45000 MPA.S AT 1%); PHENOXYETHANOL; OLIVE OIL POLYGLYCERYL-6 ESTERS; SODIUM STEAROYL LACTYLATE; TRIETHOXYCAPRYLYLSILANE

Duke Cannon Supply Co. Daily Defense Face Lotion Mineral Sunscreen Broad Spectrum SPF 32

Actrive Ingredients

Zinc Oxide 15.0%

Purpose

Sunscreen

Uses

• Helps prevent sunburn
• if used as directed with other sun protection measures (see Directions), decreases the risk of skin cancer and early skin aging caused by the sun

Warnings

For external use only

Do not use

• on damaged or broken skin

When using this product

keep out of eyes. Rinse with water to remove

Stop use and ask a doctor

• if rash occurs

Keep out of reach of children.

If swallowed, get medical help or contact a Poison Control Center right away

Directions

• Apply liberally 15 minutes before sun exposure

• Reapply: • after 80 minutes of swimming or sweating • immediately after towel drying • at least every 2 hours

- Children under 6 months of age: Ask a doctor

• Sun Protection Measures. Spending time in the sun increases your risk of skin cancer and early skin aging. To decrease this risk, regularly use a sunscreen with a Broad Spectrum SPF value of 15 or higher and other sun protection measures including:
• limit time in the sun, especially from 10 a.m. – 2 p.m. • wear long-sleeved shirts, pants, hats and sunglasses

Other information

• Protect the product in this container from excessive heat and direct sun

- May stain or damage some fabrics, materials or surfaces

Inactrive Ingredients

aloe barbadensis leaf juice, ascorbic acid, bisabolol, butyloctyl salicylate, caffeine, caprylic/capric triglyceride, cetearyl alcohol, dimethicone, ethyl ferulate, farnesol, fragrance, gluconolactone, glycerin, glyceryl stearate, helianthus annuus (sunflower) seed oil, hydroxyethyl acrylate/sodium acryloyldimethyl taurate copolymer, isohexadecane, olive oil polyglyceryl-6 esters, panax ginsing root extract, phenoxyethanol, polysorbate 60, polysorbate 80, sodium benzoate, sodium stearoyl lactylate, sorbitan isostearate, tetrasodium glutamate diacetate, tocopherol, triethoxycaprylylsilane, VP/hexadecene copolymer, water, xanthan gum